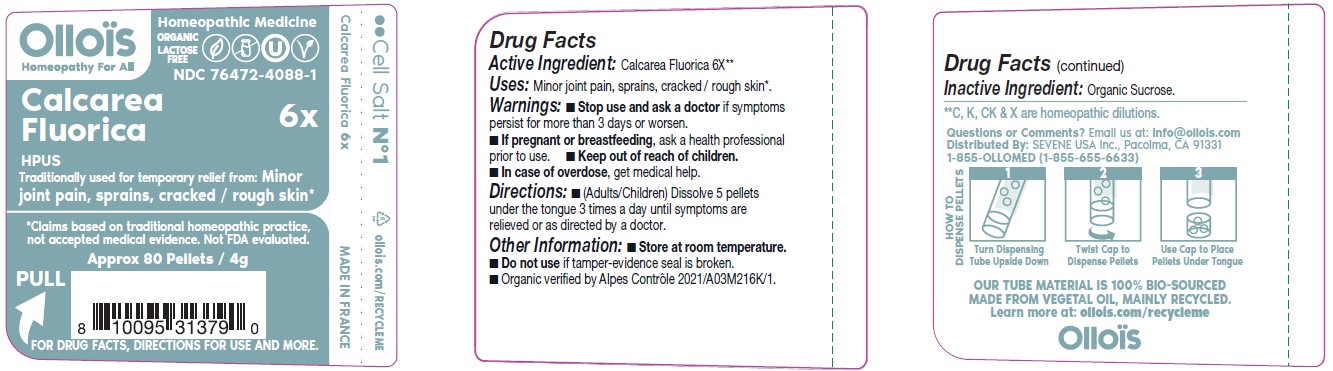 DRUG LABEL: CALCAREA FLUORICA

NDC: 76472-4088 | Form: PELLET
Manufacturer: SEVENE USA
Category: homeopathic | Type: HUMAN OTC DRUG LABEL
Date: 20250211

ACTIVE INGREDIENTS: CALCIUM FLUORIDE 6 [hp_X]/1 1
INACTIVE INGREDIENTS: SUCROSE

SEVENE USA (as PLD) - CALCAREA FLUORICA 6X (76472-4088)

ACTIVE INGREDIENT:

CALCAREA FLUORICA 6X**

**C, K, CK & X are homeopathic dilutions.

TRADITIONALLY USED FOR TEMPORARY RELIEF FROM:

Minor joint pain, sprains, cracked / rough skin*

*Claims based on traditional homeopathic practice, not accepted medical evidence. Not FDA evaluated.

DIRECTIONS:

- (Adults/Children) Dissolve 5 pellets under the tongue three times a day until symptoms are relieved or as directed by a doctor.

USES:

Minor joint pain, sprains, cracked / rough skin*.

WARNINGS

- Stop use and ask a doctor if symptoms persist for more than 3 days or worsen.

PREGNANCY OR BREAST FEEDING

- If pregnant or breast-feeding, ask a health professional before use.

- Keep out of reach of children.
- In case of overdose, get medical help.

OTHER INFORMATION:

- Store at room temperature.
- Do not use if tamper-evidence seal is broken.
- Organic verified by Alpes Control 2021/A03M216K/1.

INACTIVE INGREDIENT:

ORGANIC SUCROSE

QUESTIONS OR COMMENTS?

Email us at: info@ollois.com